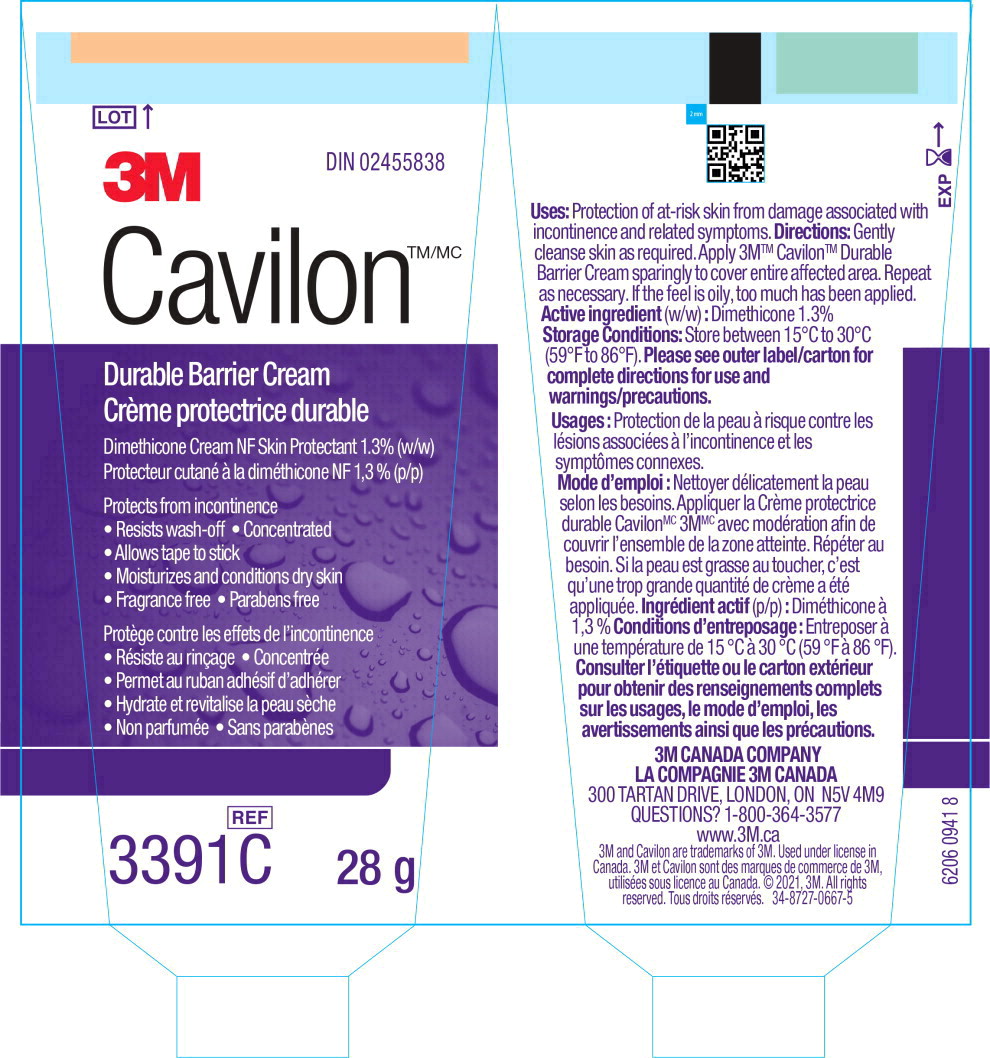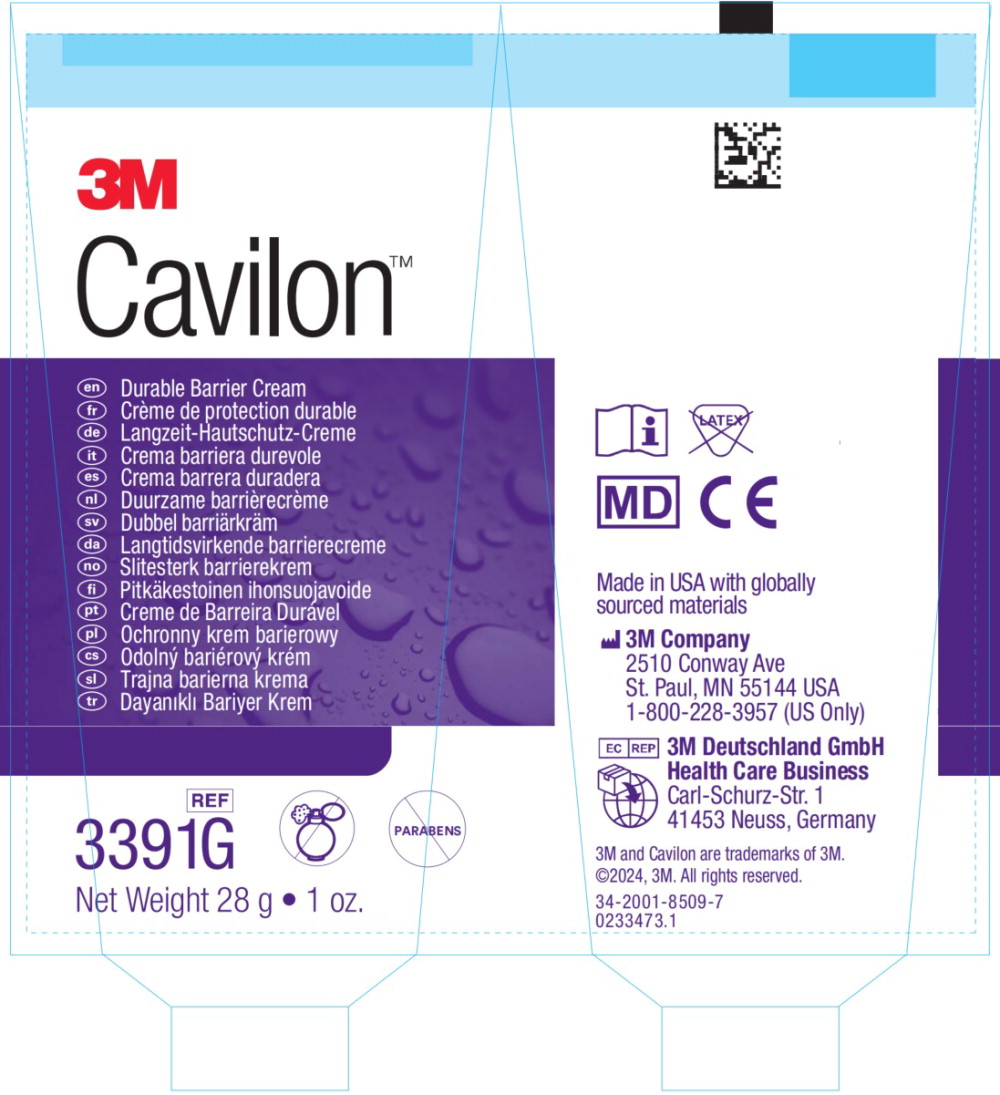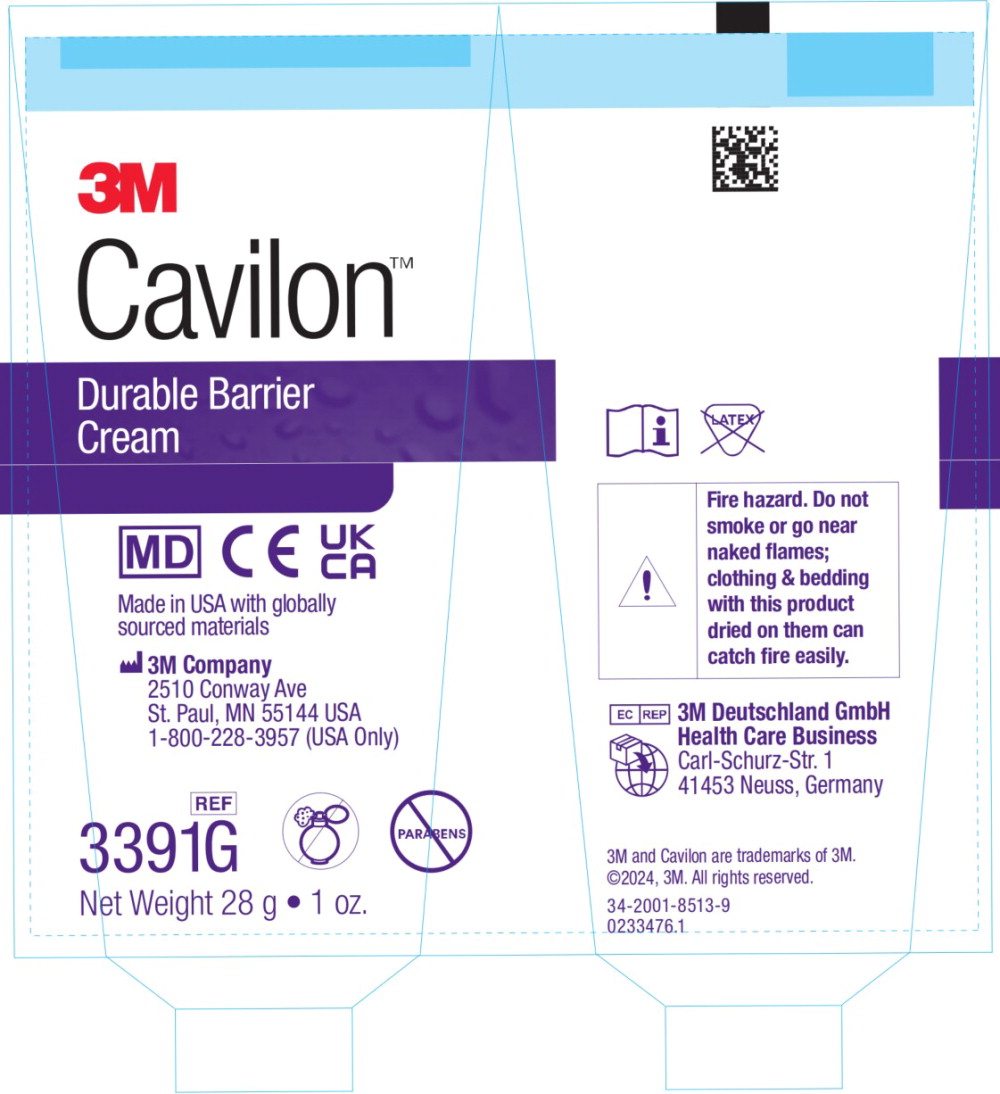 DRUG LABEL: 3M Cavilon Durable Barrier
NDC: 17518-030 | Form: CREAM
Manufacturer: Solventum US LLC
Category: otc | Type: HUMAN OTC DRUG LABEL
Date: 20251209

ACTIVE INGREDIENTS: Dimethicone 13000 mg/1 L
INACTIVE INGREDIENTS: Benzoic Acid; Coconut Oil; Dehydroacetic Acid; Diisooctyl Adipate; Glycerin; Isopropyl Palmitate; Magnesium Sulfate Heptahydrate; Mineral Oil; Paraffin; Phenoxyethanol; PPG-15 Stearyl Ether; Water

Drug Facts - CA Tube Label (28g)

Uses:

Protection of at-risk skin from damage associated with incontinence and related symptoms.

Directions:

Gently cleanse skin as required. Apply 3M™ Cavilon™ Durable Barrier Cream sparingly to cover entire affected area. Repeat as necessary. If the feel is oily, too much has been applied.

Active ingredient (w/w) : Dimethicone 1.3%

Storage Conditions:

Store between 15°C to 30°C (59°F to 86°F). Please see outer label/carton for complete directions for use and warnings/precautions.

Usages :

Protection de la peau à risque contre les lésions associées à l'incontinence et les symptômes connexes.

Mode d'emploi :

Nettoyer délicatement la peau selon les besoins. Appliquer la Crème protectrice durable CavilonMC 3MMC avec modération afin de couvrir l'ensemble de la zone atteinte. Répéter au besoin. Si la peau est grasse au toucher, c'est qu'une trop grande quantité de crème a été appliquée.

Ingrédient actif (p/p) : Diméthicone à 1,3 %

Conditions d'entreposage :

Entreposer à une température de 15 °C à 30 °C (59 °F à 86 °F). Consulter l'étiquette ou le carton extérieur pour obtenir des renseignements complets sur les usages, le mode d'emploi, les avertissements ainsi que les précautions.

3M CANADA COMPANY

LA COMPAGNIE 3M CANADA

300 TARTAN DRIVE, LONDON, ON N5V 4M9

QUESTIONS? 1-800-364-3577

www.3M.ca

3M and Cavilon are trademarks of 3M. Used under license in Canada. 3M et Cavilon sont des marques de commerce de 3M, utilisées sous licence au Canada. © 2021, 3M. All rights reserved. Tous droits réservés. 34-8727-0667-5

Principal Display Panel – CA Tube Label (28g)

LOT

3M

DIN 02455838

Cavilon™/MC

Durable Barrier Cream
Crème protectrice durable

Dimethicone Cream NF Skin Protectant 1.3% (w/w)

Protecteur cutané à la diméthicone NF 1,3 %(p/p)

Protects from incontinence

- Resists wash-off •Concentrated
- Allows tape to stick
- Moisturizes and conditions dry skin
- Fragrance free •Parabens free

Protège contre les effets de l'incontinence

- Résiste au rinçage • Concentrée
- Permet au ruban adhésif d'adhérer
- Hydrate et revitalise la peau sèche
- Non parfumée • Sans parabènes

REF

3991C 28g

Principal Display Panel – EU Tube Label (28g)

LOT

3M

CavilonTM

En Durable Barrier Cream

REF

3391G

Net Weight 28g -1oz.

Principal Display Panel – UKCA Tube Label (28g)

LOT

3M

CavilonTM

Durable Barrier Cream

REF

3391G

Net Weight 28g -1oz.